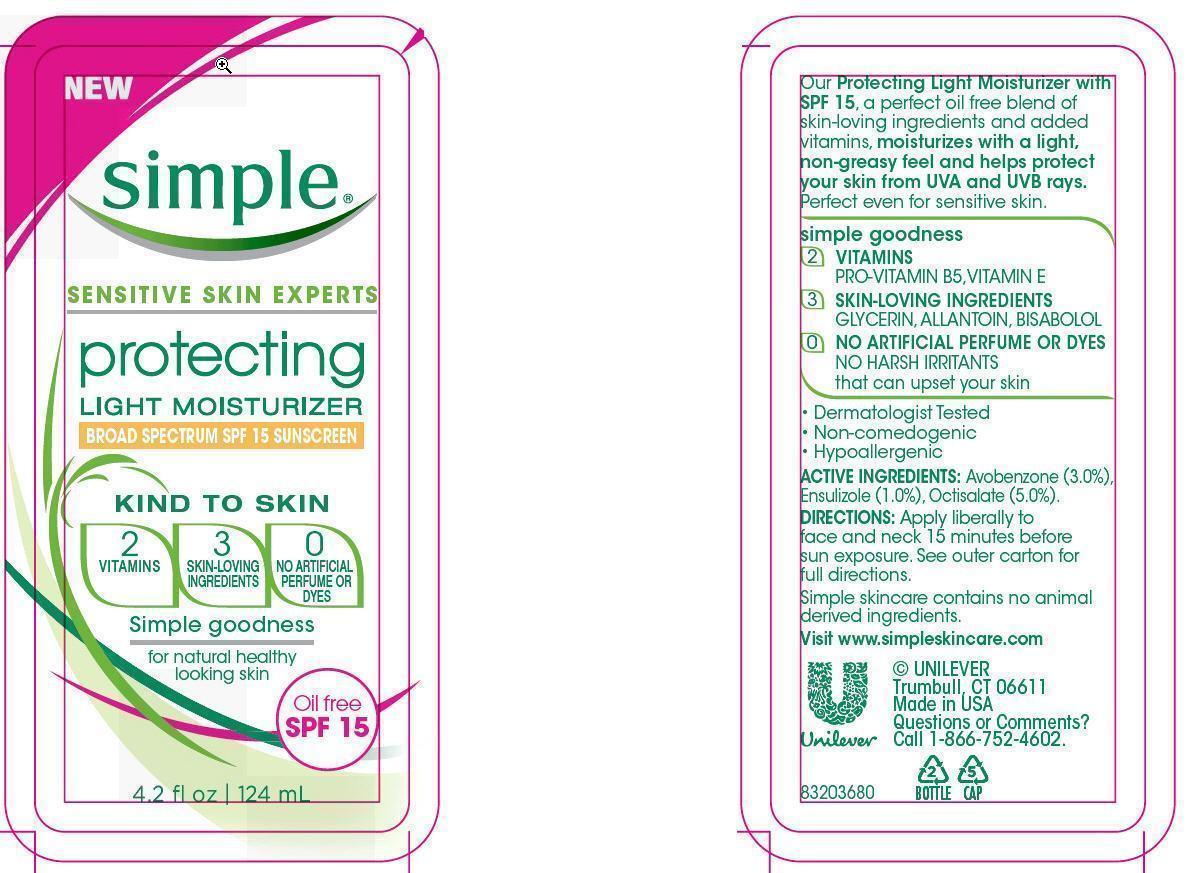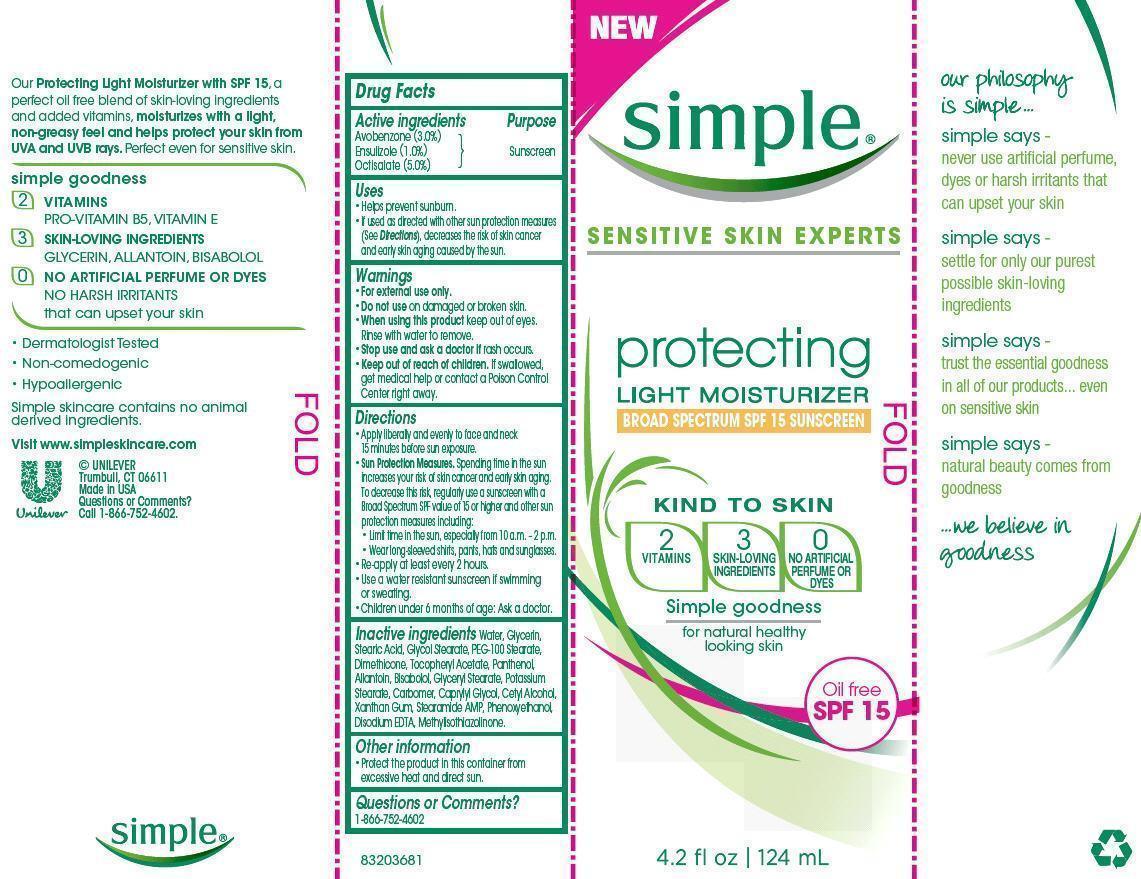 DRUG LABEL: Simple
NDC: 64942-1290 | Form: LOTION
Manufacturer: CONOPCO Inc. d/b/a Unilever
Category: otc | Type: HUMAN OTC DRUG LABEL
Date: 20130219

ACTIVE INGREDIENTS: AVOBENZONE 3.0 g/100 mL; ENSULIZOLE 1.0 g/100 mL; OCTISALATE 5.0 g/100 mL
INACTIVE INGREDIENTS: WATER; GLYCERIN; STEARIC ACID; GLYCOL STEARATE; PEG-100 STEARATE; DIMETHICONE; METHYLISOTHIAZOLINONE; POTASSIUM STEARATE; GLYCERYL MONOSTEARATE; CAPRYLYL GLYCOL; CETYL ALCOHOL; XANTHAN GUM; STEARAMIDE AMP; .ALPHA.-TOCOPHEROL ACETATE, D-; PHENOXYETHANOL; EDETATE DISODIUM; PANTHENOL; ALLANTOIN; LEVOMENOL

Simple Protecting Light Moisturizer SPF 15

Active Ingredients
AVOBENZONE (3.0%)
ENSULIZOLE (1.0%)
OCTISALATE (5.0%)

Purpose
Sunscreen

Uses
· helps prevent sunburn.
· if used as directed with other sun protection measures (see Directions), decreases the risk of skin cancer and early skin aging caused by the sun.

Warnings
· For external use only.

· Do not use on damaged or broken skin.

· When using this product keep out of eyes. Rinse with water to remove.

· Stop use and ask a doctor if rash occurs.

· Keep out of reach of children. If swallowed, get medical help or contact a Poison Control Center right away.

Directions
· apply liberally and evenly to face and neck 15 minutes before sun exposure.
Sun Protection Measures. Spending time in the sun increases your risk of skin cancer and early skin aging. To decrease this risk, regularly use a sunscreen with a Broad Spectrum SPF value of 15 or higher and other sun protection measures including:
· limit time in the sun, especially from 10a.m. - 2p.m.
· wear long-sleeved shirts, pants, hats, and sunglasses.
· re-apply at least every 2 hours.
· use a water resistant sunscreen if swimming or sweating.
· Children under 6 months of age: Ask a doctor.

Inactive ingredients
Water
Glycerin
Stearic Acid
Glycol Stearate
PEG-100 Stearate
Dimethicone
Tocopheryl Acetate
Panthenol
Allantoin
Bisabolol
Glyceryl Stearate
Potassium Stearate
Carbomer
Caprylyl Glycol
Cetyl Alcohol
Xanthan Gum
Stearamide AMP
Phenoxyethanol
Disodium EDTA
Methylisothiazolinone

Questions or comments?
Call toll free 1-866-752-4602

PACKAGE LABEL

PDP

PACKAGE LABEL

Carton